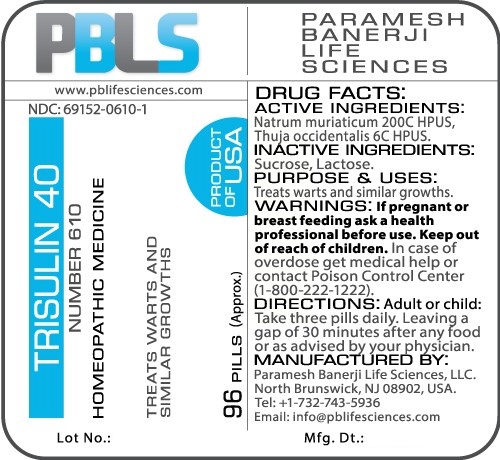 DRUG LABEL: Trisulin 40 Number 610
NDC: 69152-0610 | Form: PELLET
Manufacturer: Paramesh Banerji Life Sciences LLC
Category: homeopathic | Type: HUMAN OTC DRUG LABEL
Date: 20161114

ACTIVE INGREDIENTS: SODIUM CHLORIDE 200 [hp_C]/1 1; THUJA OCCIDENTALIS LEAFY TWIG 6 [hp_C]/1 1
INACTIVE INGREDIENTS: SUCROSE; LACTOSE

DRUG FACTS: Active Ingredients

Natrum muriaticum 200C HPUS, Thuja occidentalis 6C HPUS

Inactive Ingredients

Sucrose, Lactose

Purpose

Treats warts and similar growths

Uses

Treats warts and similar growths

Warnings

If pregnant or breast feeding ask a health professional before use.

Keep out of reach of children. In case of overdose, get medical help or contact a Poison Control Center (1-800-222-1222) right away.

Direction

Adult or child: Take three pills daily. Leaving a gap of 30 minutes after any food or as advised by your physician.

Manufactured by

Paramesh Banerji Life Sciences, LLC.

North Brunswick, NJ 08902, USA.

Tel: +1-732-743-5936

Email: info@pblifesciences.com

Principal Display Panel

NDC: 69152-0610-1

Trisulin 40

Number 610

Homeopathic Medicine

Treats warts and similar growths

96 Pills (Approx.)

Product of USA